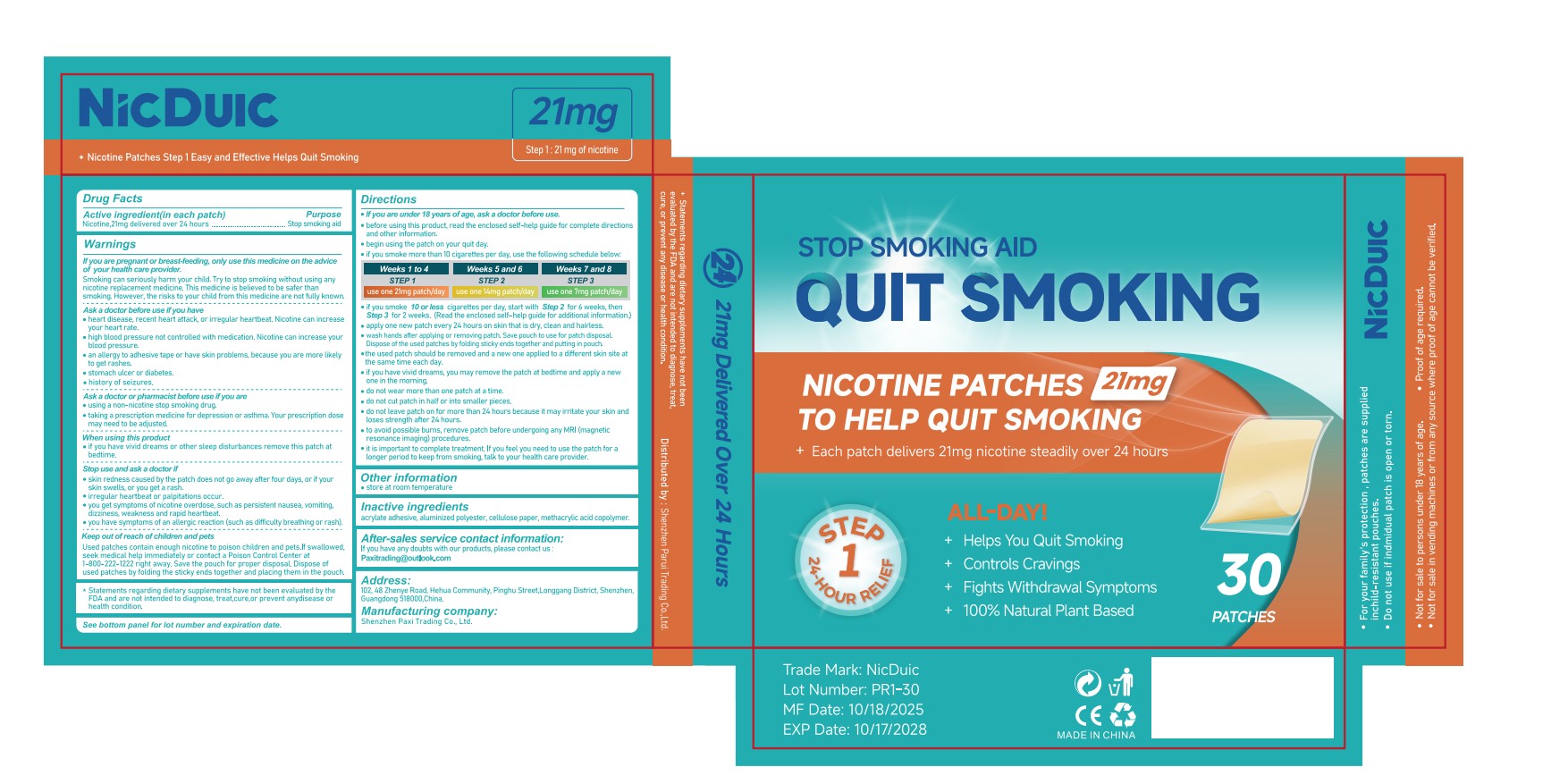 DRUG LABEL: NicDuic Quit Smoking Nicotine Patches 1 Step
NDC: 85835-012 | Form: PATCH
Manufacturer: Shenzhen Paxi Trading Co., Ltd.
Category: otc | Type: HUMAN OTC DRUG LABEL
Date: 20251122

ACTIVE INGREDIENTS: NICOTINE 21 mg/100 1
INACTIVE INGREDIENTS: METHACRYLIC ACID - METHYL METHACRYLATE COPOLYMER (1:1); ACRYLIC ACID; POLYESTER-7; POWDERED CELLULOSE

85835-012

Active Ingredient

Nicotine 21mg

Purpose

Stopsmoking aid

Use

reduces withdrawal symptoms, including nicotine craving, associated with quitting smoking.

Apply one new patch every 24 hours on skin that is dry, clean and hairless.
Remove backing from patch and immediately press onto skin. Hold for 10 seconds.
Wash hands after applying or removing patch. Save pouch to use for patch disposal. Dispose of the used patches by folding sticky ends together and putting in pouch.
The used patch should be removed and a new one applied to a different skin site at the same time each day.
If you have vivid dreams, you may remove the patch at bedtime and apply a new one in the morning.
Do not wear more than one patch at a time.
Do not cut patch in half or into smaller pieces.
Do not leave patch on for more than 24 hours because it may irritate your skin and loses strength after 24 hours.
To avoid possible burns, remove patch before undergoing any MRI (magnetic resonance imaging) procedures.
It is important to complete treatment. If you feel you need to use the patch for a longer period to keep from smoking, talk to your healthcare provider.

Warnings

If you are pregnant or breast feeding, only use this medicine on the advice of your health care provider.
Smoking can seriously harm your child. Try to stop smoking without using any nicotine replacement medicine. This medicine is believed to be safer than smoking. However, the risks to your child from this medicine are not fully known.

Do not use

Ask a doctor before use if you have
- heat disease, recent heart attack, or irregular heartbeat.Nicotine can increase your heart rate.
- high blood pressure not controlled with medication. Nicotine can increase your blood pressure.
- an allergy to adhesive tape or have skin problems, because you are more likely to get rashes.
- Stomach ulcer or diabetes.
- History of seizures.

Ask Doctor

Ask a doctor or pharmacist before use if you are
- using a non-nicotine stop smoking drug.
- taking a prescription medicine for depression or asthma. Your prescription dose may need to be adjusted.

When Using

When using this product
- if you have vivid dreams or other sleep disturbances remove this patch at bedtime.

Stop Use

Stop use and ask a doctor if
- skin redness caused by the patch does not go away after four days, or if your skin swells, or you get a rash.
- irregular heartbeat or palpitations occur.
- you get symptoms of nicotine overdose, such as persistent nausea, vomiting, dizziness, weakness and rapid heartbeat.
- You have symptoms of an allergic reaction (such as difficulty breathing or rash).

Keep out of reach of children and pets
Used patches contain enough nicotine to poison children and pets. If swallowed, seek medical help immediately or contact a Poison Control Center 1-800-222-1222 right away. Save the pouch for patch disposal. Dispose of used patches by folding the sticky ends together and placing them in the pouch.

Directions

If you are under 18 years of age, ask a doctor before use.
Before using this product, read the enclosed self–help guide for complete directions and other information.
Begin using the patch on your quit day.
If you smoke more than 10 cigarettes per day, use the following schedule below:

Weeks 1 to 4
STEP 1
use one 2lmg patch/day

Weeks 5 and 6
STEP 2
use one 14 mg patch/day

Weeks 7 and 8
STEP 3
use one 7mg patch/day

If you smoke 10 orless cigarettes per day, start with Step 2 for 6 weeks,then Step 3 for 2 weeks. (Read the enclosed self–help guide for additional information.)
Apply one new patch every 24 hours on skin that is dry, clean and hairless.
Wash hands after applying or removing patch. Save pouch to use for patch disposal. Dispose of the used patches by folding sticky ends together and putting in pouch.
The used patch should be removed and a new one applied to a different skin site at the same time each day.
If you have vivid dreams, you may remove the patch at bedtime and apply a new one in the morning.
Do not wear more than one patch at a time.
Do not cut patch in half or into smaller pieces.
Do not leave patch on for more than 24 hours because it may irritate your skin and loses strength after 24 hours.
To avoid possible burns, remove patch before undergoing any MRI (magnetic resonance imaging) procedures.
It is important to complete treatment. If you feel you need to use the patch for a longer period to keep from smoking, talk to your healthcare provider.

Other information

Store at room temperature

Inactive ingredients

acrylate adhesive, aluminized polyester,cellulose paper, methacrylic acid copolymer.

Questions

After-sales service contact information:
For any product inquiries, contact us: ParuiTrade@outlook.com